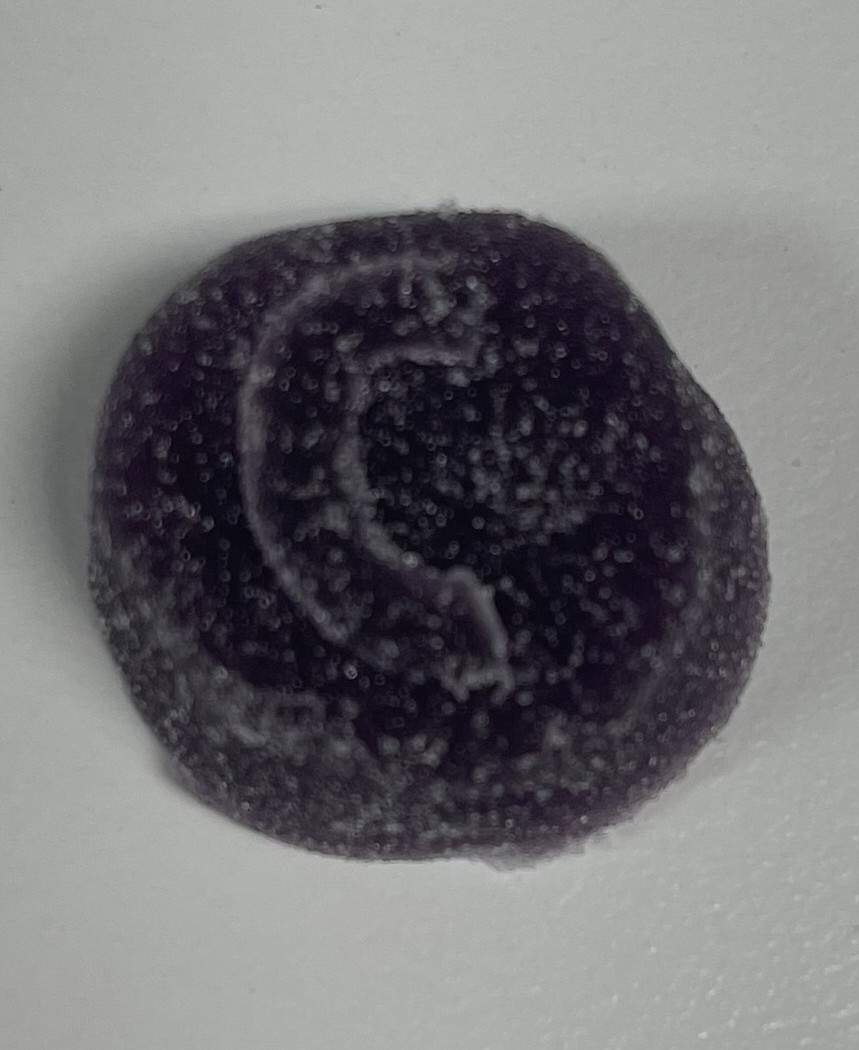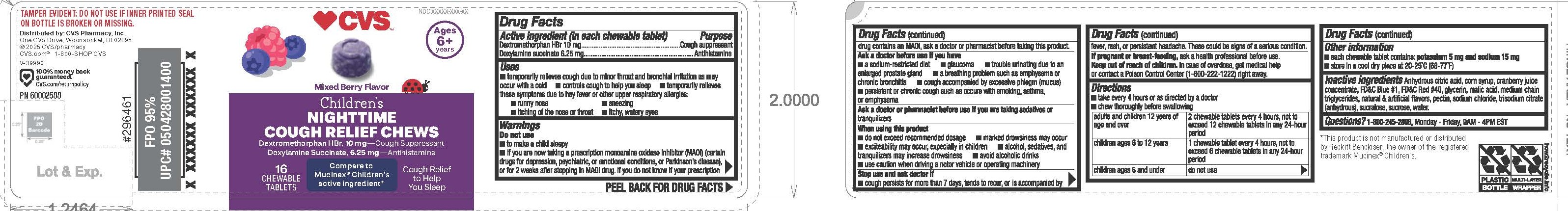 DRUG LABEL: CVS Dex-Dox Kids Nighttime Cough Suppressant
NDC: 51316-081 | Form: CHEWABLE GEL
Manufacturer: CVS
Category: otc | Type: HUMAN OTC DRUG LABEL
Date: 20250304

ACTIVE INGREDIENTS: DOXYLAMINE SUCCINATE 6.25 mg/1 1; DEXTROMETHORPHAN HYDROBROMIDE 10 mg/1 1
INACTIVE INGREDIENTS: WATER

Dextromethorphan HBr 10 mg
Doxylamine Succinate 6.25 mg

Active ingredient (in each chewable tablet)

Dextromethorphan HBr 10 mg

Doxylamine succinate 6.25 mg

Purpose

Cough suppressant

Antihistamine

Uses

- temporarily relieves cough due to minor throat and bronchial irritation as may occur with a cold
- controls cough to help you sleep
- temporarily relieves these symptoms due to hay fever or other upper respiratory allergies:
- runny nose
- itching of the nose and throat
- sneezing
- itchy, watery eyes

Warnings

Do not use

- to make a child sleep
- if you are now taking a prescription monoamine oxidase inhibitor (MAOI) (certain drugs for depression, psychiatric, or emotional conditions, or Parkinson's disease), or for 2 week after stopping an MAOI drug. If you do not know if your prescription drug contains an MAOI, ask a doctor or pharmacist before taking this product.

Ask a doctor before use if you have

- a sodium-restricted diet
- glaucoma
- trouble urinating due to an enlarged prostate gland
- a breathing problem such as emphysema or chronic bronchitis
- cough accompanied by excessive phlegm (mucus)
- persistent or chronic cough such as occurs with smoking, asthma, or emphysema

Ask a doctor or pharmacist before use if you are taking sedatives or tranquilizers

When using this product

- do not exceed recommended dosage
- marked drowsiness may occur
- exciteability may occur, expecially in children
- alcohol, sedatives, and tranquilizers may increase drowsiness
- avoid alcoholic drings
- use caution when driving a motor vehicle or operating machinery

Stop use and ask doctor if

- cough persists for more than 7 days, tends to recur, or is accompanied by fever, rash, or persistent headache. These could be signs of a serious condition.

PREGNANCY OR BREAST FEEDING

If pregnant or breast-feeding, ask a health professional before use.

Keep out of reach of children.

OVERDOSAGE

In case of overdose, get medical help or contact a Poison Control Center (1-800-222-1222) right away.

Directions

- take every 4 hours or as directed by a doctor
- chew thoroughly before swallowing

adults and children 12 years of age and over - 2 chewable tablets every 4 hours, not to exceed 12 chewable tablets in any 24-hour period

children ages 6 to 12 years - 1 chewable tablet every 4 hours, not to exceed 6 chewable tablets in any 24-hour period

children ages 6 and under - do not use

Other information

- each chewable tablet contains: potassium 5 mg and sodium 15 mg
- store in a cool dry place at 20° - 25°C (68° - 77°F)

INACTIVE INGREDIENT

Inactive ingredients: Anhydrous citric acid, corn syrup, cranberry juice concentrate, FD&C Blue #1, FD&C Red #40, glycerin, malic acid, medium chain triglycerides, natural & artificial flavors, pectin, sodium chloride, trisodium citrate (anhydrous), sucralose, sucrose, water.

QUESTIONS

Questions? 1-800-245-2898, Monday - Friday, 9AM - 4PM EST